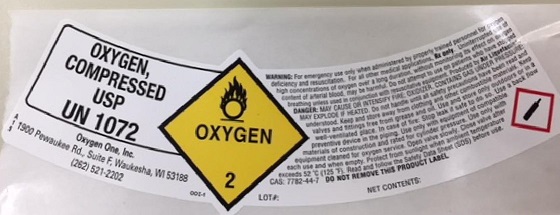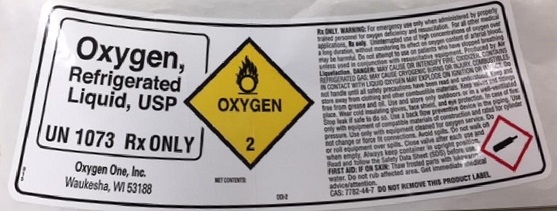 DRUG LABEL: Oxygen
NDC: 65689-001 | Form: GAS
Manufacturer: Oxygen One, Inc.
Category: prescription | Type: HUMAN PRESCRIPTION DRUG LABEL
Date: 20191018

ACTIVE INGREDIENTS: OXYGEN 992 mL/1 L

oxygen

PACKAGE LABEL

OXYGEN, COMPRESSED USP UN1072 OXYGEN 2
WARNING: For emergency use only when administered by properly trained personnel for oxygen deficiency and resuscitation. For all other medical application, Rx only. Uninterrupted use of high concentrations of oxygen over a long duration, without monitoring its effect on oxygen content of arterial blood, may be harmful. Do not attempt to use on patients who have stopped breathing unless used in conjunction with resuscitative equipment. PRODUCED BY AIR LIQUIFACTION DANGER: MAY CAUSE OR INTENCIFY FIRE; OXYDIZER. CONTAINS GAS UNDER PRESSURE; MAY EXPLODE IF HEATED. Do not handle until all safety precautions have been read and understood. Keep and store away from clothing and other combustible materials. Keep valves and fittings free from grease and oil. Use and store only outdoors or in a well-ventilated place. In case of fire; Stop leak if safe to do so. Use a back flow preventive device in the piping. Use only with equipment of compatible materials of construction and rated for cylinder pressure. Use only with equipment cleaned for oxygen service. Open valve slowly. Close valve after each use and when empty. Protect from sunlight when ambient temperature exceeds 52 C (125 F). Read and follow the Safety Data Sheet (SDS) before use. CAS: 7782-44-7 DO NOT REMOVE THIS PRODUCT LABEL
Oxygen One, Inc. 1900 Pewaukee Rd., Suite F, Waukesha, Wi 53188 (262) 521-2202

PACKAGE LABEL

OXYGEN, REFRIGERATED LIQUID USP UN1073 Rx ONLY OXYGEN 2Rx ONLY.
WARNING: USP For emergency use only when administered by properly trained personnel for oxygen deficiency and resuscitation. For all other medical applications, Rx only. Uninterrupted use of high concentrations of oxygen over a long duration, without monitoring its effect on oxygen content of arterial blood, may be harmful. Do not attempt to use on patients who have stopped breathing unless used in conjunction with resuscitative equipment. Produced by Air Liquefaction.
DANGER: MAY CAUSE OR INTENSIFY FIRE; OXYDIZER. CONTAINS REFRIGERATED GAS; MAY CAUSE CRYOGENIC BURNS OR INJURY. COMBUSTIBLES IN CONTACT WITH LIQUID OXYGEN MAY EXPLODE ON IGNITION OR IMPACT. Do not handle until all safety precautions have been read and understood. Keep and store away from clothing and other combustible materials. Keep valves and fittings free from grease and oil. Use and store only outdoors or in a well-ventilated place. Wear cold insulating gloves, face shield, and eye protection. In case of fire; Stop leak if sfe to do so. Use a back flow preventive device inthe piping. Use only with equipment of compatible materials of construction and rated for cylinder pressure. Use only with equipment cleaned for oxygen service. DO NOT change or force fit connections. Avoid spills, Do not walk on or foll equipment over spills. Close valve after each use and when empty. Always keep container in upright position. Read and follow the Safety Data Sheet (SDS) before use.
FIRST AID: IF ON SKIN: Thaw frosted parts with lukewarm water. Do not rub affected area. Get immediate medical advice/attention. DO NOT REMOVE THIS PRODUCT LABEL. CAS: 7782-44-7
Oxygen One, Inc. 1900 Pewaukee Rd., Suite F, Waukesha, Wi 53188 (262) 521-2202